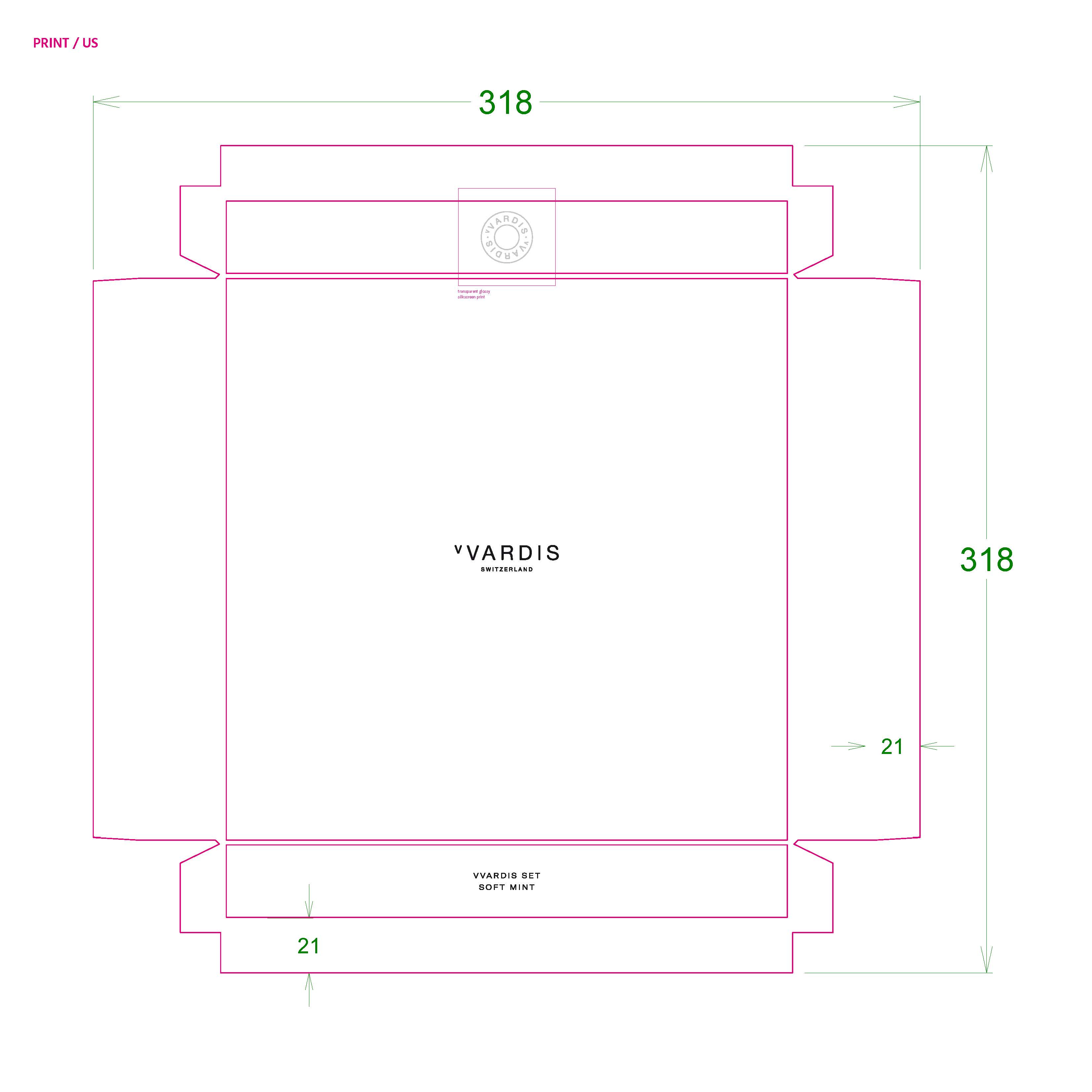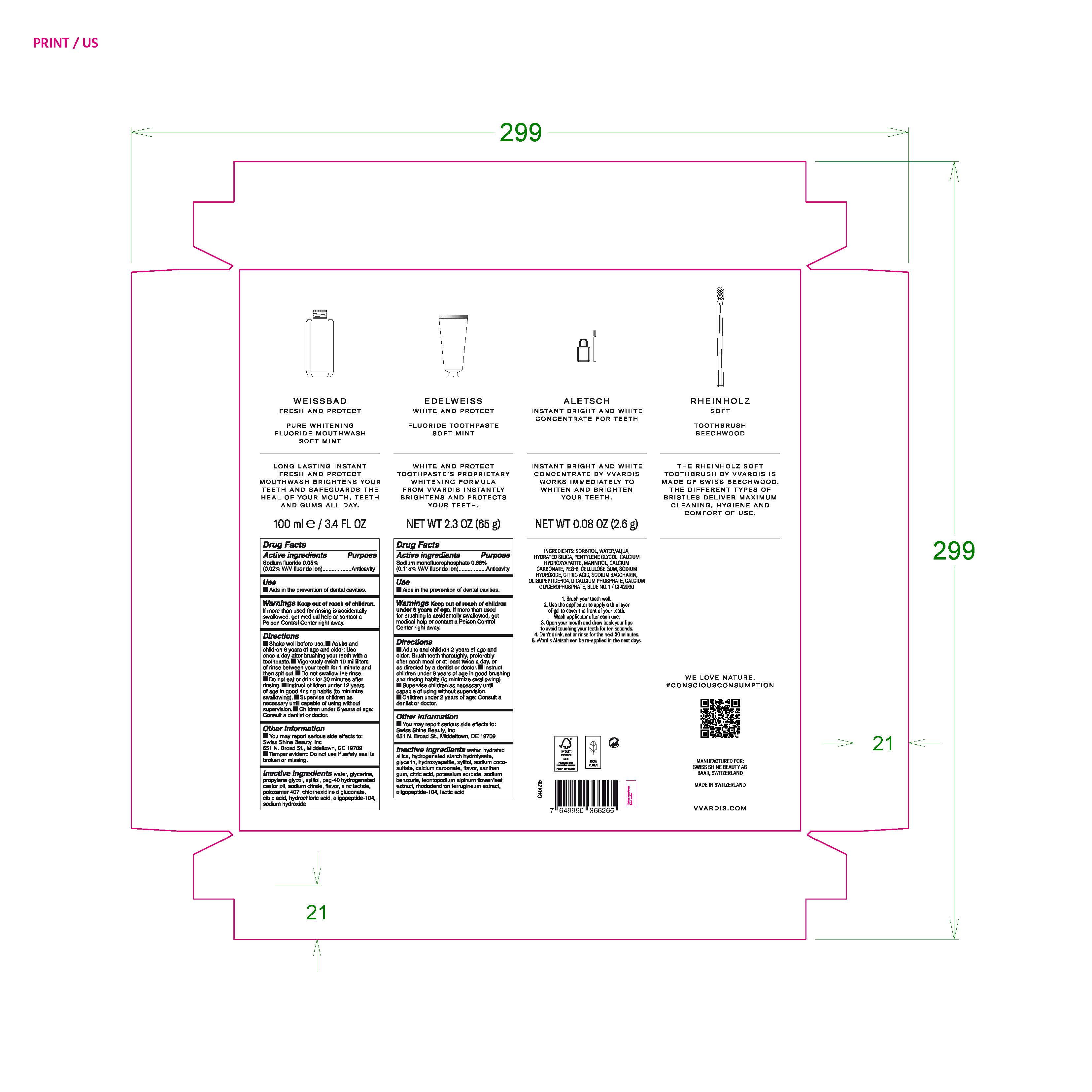 DRUG LABEL: VVARDIS SET SOFT MINT
NDC: 79763-004 | Form: KIT | Route: ORAL
Manufacturer: Swiss Shine Beauty AG
Category: otc | Type: HUMAN OTC DRUG LABEL
Date: 20210819

ACTIVE INGREDIENTS: SODIUM FLUORIDE 0.05 g/100 mL; SODIUM MONOFLUOROPHOSPHATE 0.88 g/100 g
INACTIVE INGREDIENTS: POLOXAMER 407; CHLORHEXIDINE GLUCONATE; SODIUM HYDROXIDE; HYDROCHLORIC ACID; WATER; POLYOXYL 40 HYDROGENATED CASTOR OIL; PROPYLENE GLYCOL; XYLITOL; SODIUM CITRATE; ZINC LACTATE; CITRIC ACID MONOHYDRATE; GLYCERIN; XYLITOL; CALCIUM CARBONATE; XANTHAN GUM; CITRIC ACID MONOHYDRATE; SODIUM BENZOATE; TRIBASIC CALCIUM PHOSPHATE; LEONTOPODIUM ALPINUM FLOWERING TOP; RHODODENDRON FERRUGINEUM WHOLE; LACTIC ACID; WATER; HYDROGENATED STARCH HYDROLYSATE; GLYCERIN; HYDRATED SILICA; SODIUM COCO-SULFATE; POTASSIUM SORBATE

VVARDIS SET SOFT MINT

Active Ingredients

Sodium fluoride 0.05% (0.02% W/V fluoride ion)

Purpose Anticavity

Active Ingredients

Sodium monofluorophosphate 0.88% (0.115% W/V flouride ion)

Purpose Anticavity

Use

Aids in the prevention of dental cavities.

KEEP OUT OF REACH OF CHILDREN

Warnings Keep out of reach of children. If more than used for rinsing is accidentally swallowed, get medical help or contact a Poison Control Center right away.

KEEP OUT OF REACH OF CHILDREN

Warnings Keep out of reach of children under 6 years of age. If more than used for brushing is accidentally swallowed, get medical help or contact a Poison Control Center right away.

INDICATIONS AND USAGE

Supervise children as necessary until capable of using without supervison.

Children under 2 years of age: Consult a dentist or doctor.

INDICATIONS AND USAGE

Supervise children as necessary until capable of using without supervision.

Children under 6 years of age: Consult a dentist or doctor.

WARNINGS

Warnings Keep out of reach of children. If more than used for rinsing is accidently swallowed, get medical help or contact a Poison Control Center right away.

WARNINGS

Warnings Keep out of reach of children under 6 years of age. If more than used for brushing is accidentally swallowed, get medical help or contact a Poison Control Center right away.

Directions

- Shake well before use.
- Adults and children 6 years of age and older: Use once a day after brushing your teeth with a toothpaste.
- Vigorously swish 10 milliliters of rinse between your teeth for 1 minute and then spit out.
- Do not swallow the rinse.
- Do not eat or drink for 30 minutes after rinsing.
- Instruct children under 12 years of age in good rinsing habits (to minimize swallowing).
- Supervise children as necessary until capable of using wihtout supervision.
- Children under 6 years of age: Consult a dentist or doctor.

Directions

- Adults and children 2 years of age and older: Brush teeth thoroughly, preferably after each meal or at least twice a day, or as directed by a dentist or doctor.
- Instruct children under 6 years of age in good brushing and rinsing habits (to minimize swallowing)
- Supervise children as necessary until capable of using without supervison.
- Children under 2 years of age: consult a dentist or doctor.

Inactive Ingredients

water, glycerine, propylene glycol, xylitol, peg-40 hydrogenated castor oil, sodium citrate, flavor, zinc lactate, poloxamer 407, chlorhexidine digluconate, citric acid, hydrochloric acid, oligopeptide-104, sodium hydroxide

Inactive Ingredients

water, hydrated silica, hydrogenated starch hydrolysate, glycerin, hydroxyapatite, xylitol, sodium coco-sulfate, calcium carbonate, flavor, xanthan gum, citric acid, potassium sorbate, sodium benzoate, leontopodium alpinum flower/leaf extract, rhododendron ferrugineum extract, oligopeptide-104, lactic acid.

Other information

You may report serious side effects to: Swiss Shine Beauty, Inc

651 N. Broad St., Middletown, DE 19709

Tamper evident: Do not use if safety seal is broken or missing.

PACKAGE LABEL

WEISSBAD

FRESH AND PROTECT

PURE WHITENING

FLUORIDE MOUTHWASH

SOFT MINT

100 ml e /3.4 FL OZ

EDELWEISS
WHITE AND PROTECT
FLUORIDE TOOTHPASTE
SOFT MINT

NET WT 2.3 OZ (65 g)